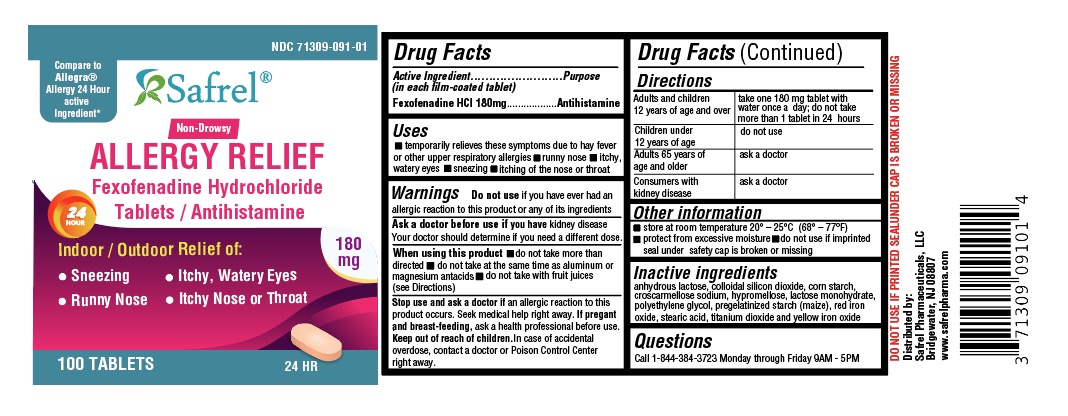 DRUG LABEL: Fexofenadine Hydrochloride
NDC: 71309-091 | Form: TABLET
Manufacturer: Safrel Pharmaceuticals, LLC.
Category: otc | Type: HUMAN OTC DRUG LABEL
Date: 20230328

ACTIVE INGREDIENTS: FEXOFENADINE HYDROCHLORIDE 180 mg/1 1
INACTIVE INGREDIENTS: CROSCARMELLOSE SODIUM; FERRIC OXIDE RED; FERRIC OXIDE YELLOW; HYPROMELLOSE, UNSPECIFIED; ANHYDROUS LACTOSE; MAGNESIUM STEARATE; MICROCRYSTALLINE CELLULOSE; POLYETHYLENE GLYCOL, UNSPECIFIED; SILICON DIOXIDE; STARCH, CORN; TITANIUM DIOXIDE; LACTOSE MONOHYDRATE

Fexofenadine HCl Tablets 180 mg

ACTIVE INGREDIENT(S)

Fexofenadine HCl USP 60 mg (for 60 mg)
Fexofenadine HCl USP 180 mg (for 180 mg)

PURPOSE

Antihistamine

USE(S)

temporarily relieves these symptoms due to hay fever or other upper respiratory allergies:

- runny nose
- itchy, water eyes
- sneezing
- itching of the nose or throat

WARNINGS

Do not use
if you have ever had an allergic reaction to this product or any of its ingredients.
Ask a doctor before use if you have
kidney disease. Your doctor should determine if you need a different dose.
When using this product

- do not take more than directed
- do not take at the same time as aluminum or magnesium antacids
- do not take with fruit juices (see Directions)

Stop use and ask a doctor if
an allergic reaction to this product occurs. Seek medical help right away.
If pregnant or breast-feeding
ask a health professional before use.

Keep out of reach of children

In case of overdose, get medical help or contact a Poison Control Center right away.

DIRECTIONS

adults and children 12 years of age and over | take one 60 mg tablet with water every 12 hours; do not take more than 2 tablets in 24 hours (for 60 mg) take one 180 mg tablet with water once a day; do not take more than 1 tablet in 24 hours (for 180 mg)
children under 12 years of age | do not use
adults 65 years of age and older | ask a doctor
consumers with kidney disease | ask a doctor

OTHER INFORMATION

- Safety-sealed: do not use if foil printed with granules logo under bottle cap is opened or torn.
- Do not use if carton is opened or if individual blister units are torn or opened.
- store between 20º and 25ºC (68º and 77ºF)
- protect from excessive moisture

INACTIVE INGREDIENTS

anhydrous lactose, colloidal silicon dioxide, corn starch, croscarmellose sodium, hypromellose, lactose monohydrate, polyethylene glycol, pregelatinized starch (maize), red iron oxide, stearic acid, titanium dioxide and yellow iron oxide

QUESTIONS OR COMMENTS

Contact 1-844-384-3723 Mon-Fri 8:00 AM EST to 5:00 PM PST
Distributed By:
Safrel Pharmaceuticals, LLC
Bridgewater, NJ 08807

PRINCIPAL DISPLAY PANEL

NDC 71309-091-01 - 100 Count